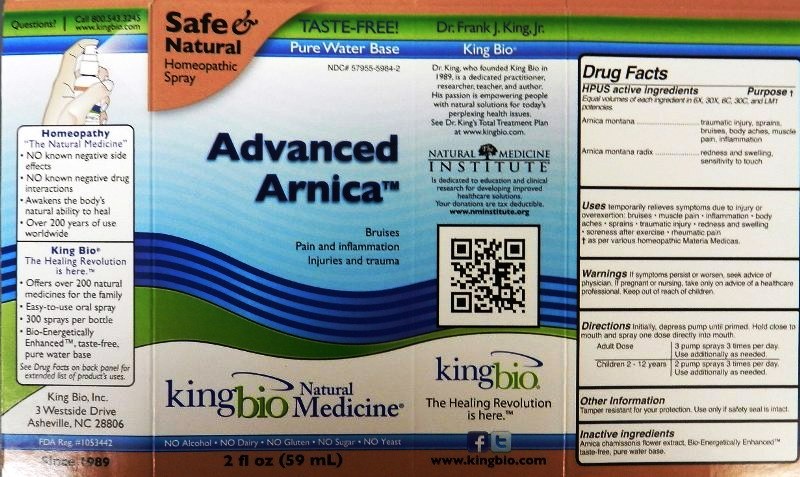 DRUG LABEL: Advanced Arnica
NDC: 57955-5984 | Form: LIQUID
Manufacturer: King Bio Inc.
Category: homeopathic | Type: HUMAN OTC DRUG LABEL
Date: 20191008

ACTIVE INGREDIENTS: ARNICA MONTANA 6 [hp_X]/59 mL; ARNICA MONTANA ROOT 6 [hp_X]/59 mL
INACTIVE INGREDIENTS: ARNICA CHAMISSONIS FLOWER; WATER

Advanced Arnica

Active Ingredients

HPUS active ingredients

Equal volumes of each ingredient in 6X, 30X, 6C, 30C, and LM1 potencies.

Arnica montana

Arnica montana radix

Reference image of arnica.jpg

Inactive Ingredients

Arnica chamissonis flower extract,

Bio-Energetically Enhanced taste-free, pure water base.

Reference image of arnica.jpg

Dosage and Administration

Directions Initially, depress pump until primed. Hold close to mouth and spray one dose directly into mouth.

Adult Dose- 3 pump sprays 3 times per day. Use additionally as needed.

Children 2-12 years- 2 pump sprays 3 times per day. Use additionally as needed.

Reference image of arnica.jpg

Purpose

HPUS active ingredients Purpose

Equal volumes of each ingredient in 6X, 30X, 6C, 30C, and LM1 potencies.

Arnica montana.......................................traumatic injury, sprains, bruises, body aches, muscle pain, inflammation

Arnica montana radix..............................redness and swelling, sensitivity to touch

Reference image of arnica.jpg

Indications and Usage

Uses temporarily relieves symptoms due to injury or overexertion:

- bruises
- muscle pain
- inflammation
- body aches
- sprains
- traumatic injury
- redness and swelling
- soreness after exercise
- rheumatic pain

as per various homeopathic Materia Medicas.
King Bio Inc.
3 Westside Drive
Asheville, NC 28806
www.kingbio.com
Reference image of arnica.jpg

Warnings

Warnings If symptoms persist or worsen, seek advice of physician. If pregnant or nursing, take only on advice of a healthcare professional. Keep out of reach of children.

Other Information Tamper resistant for your protection. Use only if safety seal is intact.

Reference image of arnica.jpg

Keep out of reach of children.

Reference image of arnica.jpg

PACKAGE LABEL

King Bio Inc.

3 Westside Drive

Asheville, NC 28806

www.kingbio.com

Reference image arnica.jpg